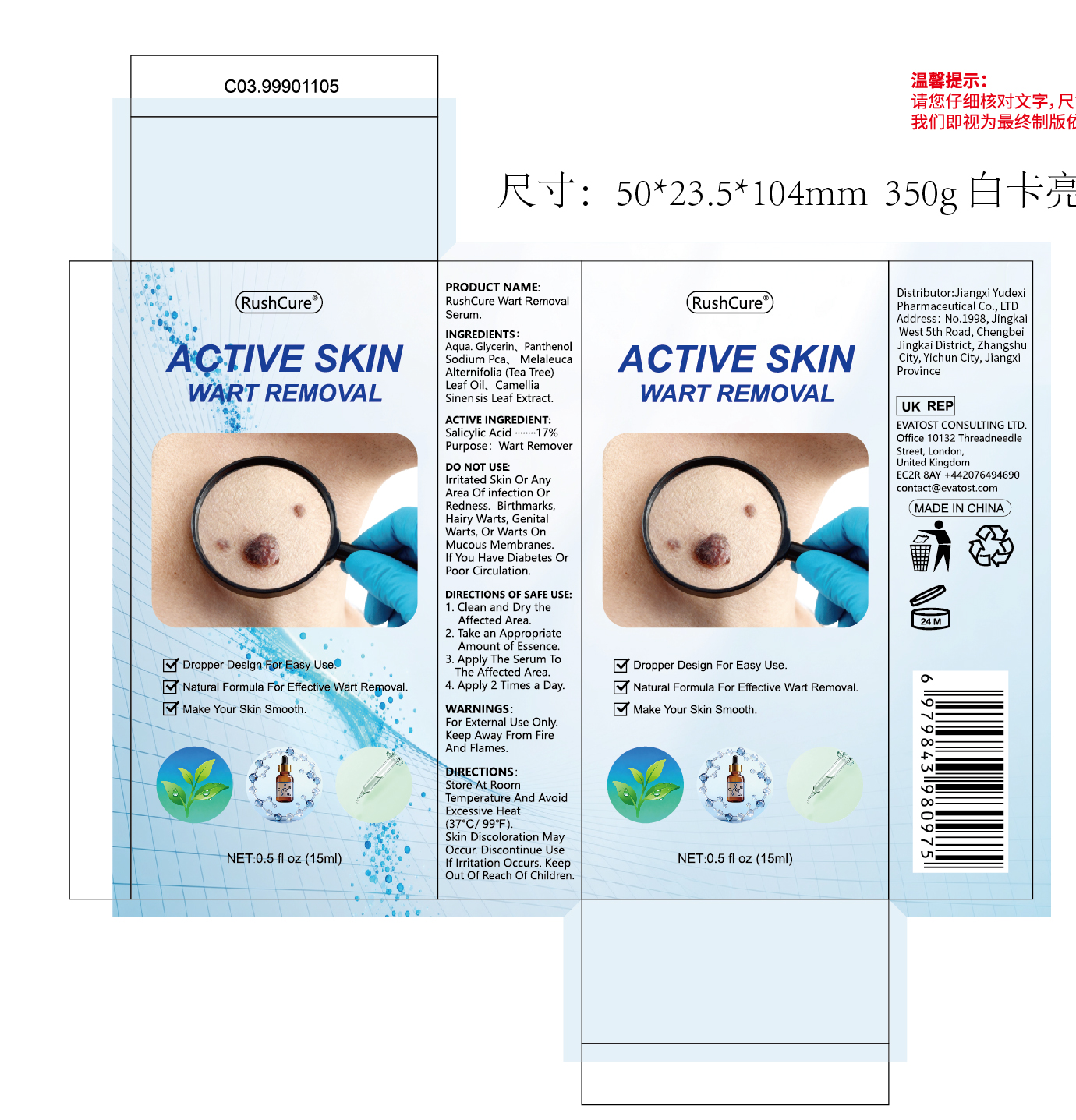 DRUG LABEL: RushCure Wart Removal Serum
NDC: 85248-085 | Form: LIQUID
Manufacturer: Jiangxi Yudexi Pharmaceutical Co., LTD
Category: otc | Type: HUMAN OTC DRUG LABEL
Date: 20260207

ACTIVE INGREDIENTS: SALICYLIC ACID 17 g/100 mL
INACTIVE INGREDIENTS: GLYCERIN; CAMELLIA SINENSIS LEAF; SODIUM PCA; PANTHENOL; WATER; MELALEUCA ALTERNIFOLIA (TEA TREE) LEAF OIL

85248-085

Active Ingredient

Salicylic acid 17%

Purpose

Wart remover

Use

1

Warnings

For External Use Only.Keep Away From Fire and Flames.

Do not use

lrrtated Skin Or Any Area Of infection Or Redness. Birthmarks,Hairy Warts, Genital Warts,Or Warts On Mucous Membranes If You Have Diabetes Or Poor Circulation.

When Using

Please keep out of reach of children.Do not swallow.Please clean your hands before use to ensure the best results from the product.Discontinue use if signs of irritation or rash occur. Store in a cool and dry place.

Stop Use

Discontinue use if signs of irritation or rash occur.

Ask Doctor

Discontinue use if signs of irritation or rash occur.

Keep Oot Of Reach Of Children

Please keep out of reach of children.Do not swallow.

Directions

1.Clean and Dry the Affected Area. 2. Take an Appropriate Amount of Essence. 3. Apply The Serum To The Affected Area. 4. Apply 2 Times a Day.

Other information

Store At Room Temperature And Avoid Excessive Heat(37°c/ 99°f).Skin Discoloration May Occur. Discontinue Use lf lrritation Occurs.Keep Out Of Reach Of Children

Inactive ingredients

Aqua.Glycerin、Pantheno Sodium Pca、Melaleuca Alternifolia (Tea Tree)Leaf Oil、Camellia Sinen-sis Leaf Extract.